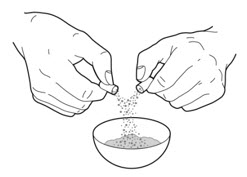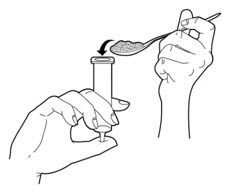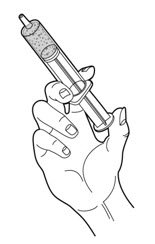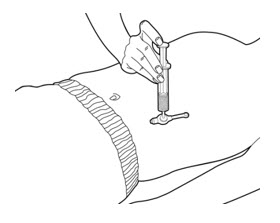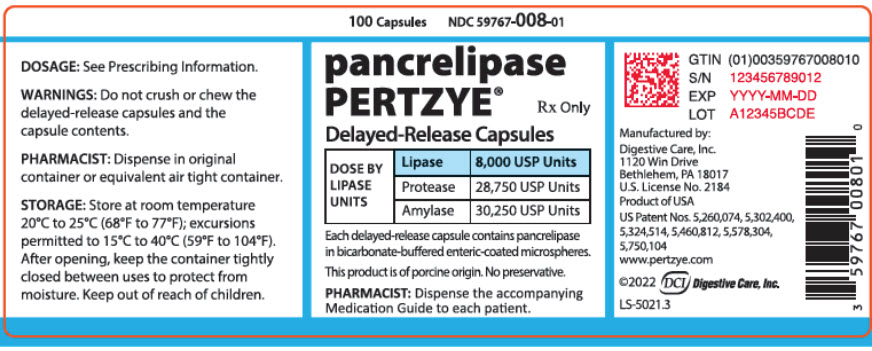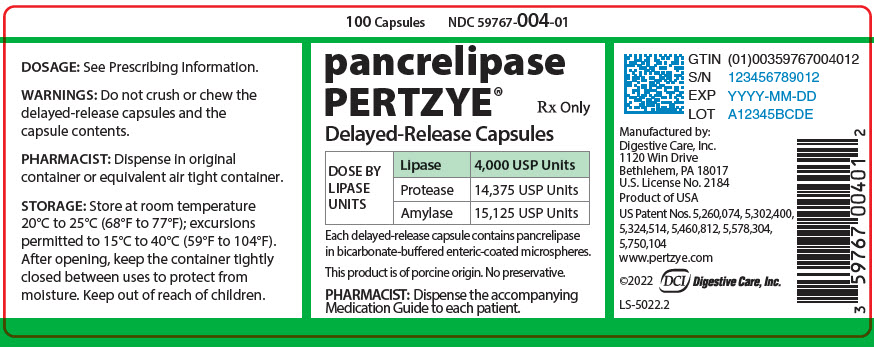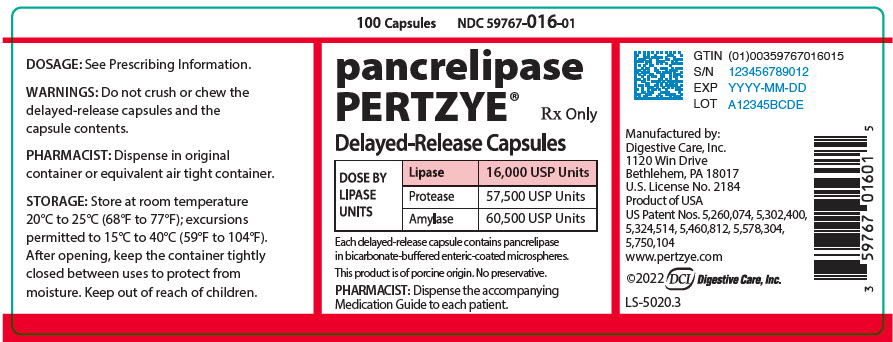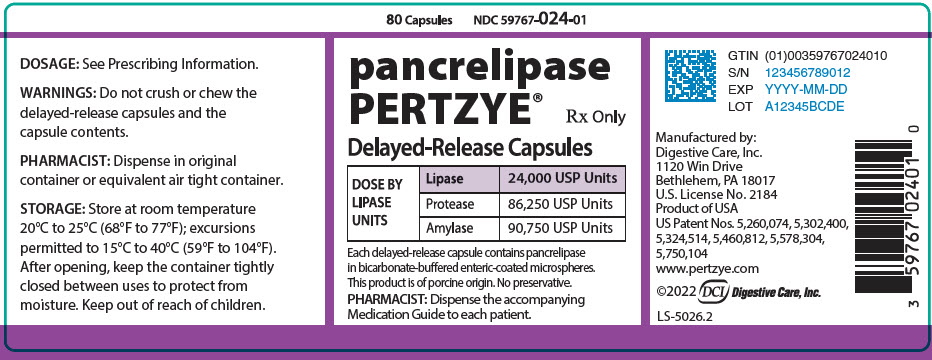 DRUG LABEL: PERTZYE
NDC: 59767-008 | Form: CAPSULE, DELAYED RELEASE
Manufacturer: Digestive Care, Inc.
Category: prescription | Type: HUMAN PRESCRIPTION DRUG LABEL
Date: 20240311

ACTIVE INGREDIENTS: PANCRELIPASE LIPASE 8000 [USP'U]/1 1; PANCRELIPASE AMYLASE 30250 [USP'U]/1 1; PANCRELIPASE PROTEASE 28750 [USP'U]/1 1
INACTIVE INGREDIENTS: CELLACEFATE; DIETHYL PHTHALATE; POVIDONE K90; SODIUM BICARBONATE; SODIUM CARBONATE; SODIUM STARCH GLYCOLATE TYPE A; TALC; URSODIOL

HIGHLIGHTS OF PRESCRIBING INFORMATION

These highlights do not include all the information needed to use PERTZYE safely and effectively. See full prescribing information for PERTZYE.
PERTZYE (pancrelipase) delayed-release capsules, for oral use
Initial U.S. Approval: 2012

1 INDICATIONS AND USAGE

PERTZYE® is indicated for the treatment of exocrine pancreatic insufficiency in adult and pediatric patients. (1)

2 DOSAGE AND ADMINISTRATION

Important Dosing Information (2.1)

- PERTZYE is a mixture of enzymes including lipases, proteases, and amylases and dosing is based on lipase units. Dosing scheme based on actual body weight or fat ingestion.
- Individualize the dosage based on clinical symptoms, the degree of steatorrhea present, and the fat content of the diet.
- Do not exceed 2,500 lipase units/kg/meal, 10,000 lipase units/kg/day, or 4,000 lipase units/g fat ingested/day in adult and pediatric patients greater than 12 months of age without further investigation. (5.1)
- The total daily dosage in adult and pediatric patients greater than 12 months of age should reflect approximately three meals plus two or three snacks per day. With each snack, administer approximately half the prescribed dose for a meal.
- Do not substitute other pancreatic enzyme products for PERTZYE. When switching from another pancreatic enzyme product to PERTZYE, monitor patients for clinical symptoms of exocrine pancreatic insufficiency and titrate the dosage as needed.

Recommended Dosage (2.2)

Adults and Pediatric Patients Greater than 12 Months: The recommended initial starting dosage is:

- 500 lipase units/kg/meal for adult and pediatric patients 4 years of age and older.
- 1,000 lipase units/kg/meal for pediatric patients greater than 12 months to less than 4 years of age.
- Titrate the dosage to either 2,500 lipase units/kg/meal, 10,000 lipase units/kg/day, or 4,000 lipase units/g fat ingested/day. Higher dosages may be administered if documented to be effective by fecal fat measures or improvement in malabsorption.

Pediatric Patients Birth to 12 Months: The recommended dosage is 4,000 lipase units (one capsule) per 120 mL of formula or per breastfeeding.

Preparation and Administration Instructions (2.3)

- Swallow capsules whole. For patients unable to swallow intact capsule(s), the capsule contents may be sprinkled on soft acidic food (e.g., applesauce).
  - The 4,000 USP lipase unit capsule may be administered with applesauce via gastrostomy tube (14 French or larger). The contents of no more than two capsules may be administered at a time.
- Do not crush or chew PERTZYE capsules or capsule contents.
- Consume sufficient liquids to ensure complete swallowing of PERTZYE. (5.2)
- See the full prescribing information for additional information on administering to pediatric patients birth to 12 months of age.

3 DOSAGE FORMS AND STRENGTHS

Delayed-Release Capsules (3):

- 4,000 USP units of lipase; 14,375 USP units of protease; and 15,125 USP units of amylase.
- 8,000 USP units of lipase; 28,750 USP units of protease; and 30,250 USP units of amylase.
- 16,000 USP units of lipase; 57,500 USP units of protease; and 60,500 USP units of amylase.
- 24,000 USP units of lipase; 86,250 USP units of protease; and 90,750 USP units of amylase.

4 CONTRAINDICATIONS

None. (4)

5 WARNINGS AND PRECAUTIONS

- Fibrosing Colonopathy: Associated with high doses, usually over prolonged use and in pediatric patients with cystic fibrosis. Colonic stricture reported in pediatric patients less than 12 years of age with dosages exceeding 6,000 lipase units/kg/meal. Monitor during treatment for progression of preexisting disease. Do not exceed the recommended dosage, unless clinically indicated. (2.1, 5.1)
- Irritation of the Oral Mucosa: May occur due to loss of protective enteric coating on the capsule contents. (5.2)
- Hyperuricemia: Reported with high dosages, consider monitoring blood uric acid levels in patients with gout, renal impairment, or hyperuricemia. (5.3)
- Risk of Viral Transmission: The presence of porcine viruses that might infect humans cannot be definitely excluded. (5.4)
- Hypersensitivity Reactions: Monitor patients with known reactions to proteins of porcine origin. If symptoms occur, initiate appropriate medical management; consider the risks and benefits of continued treatment. (5.5)

6 ADVERSE REACTIONS

Most common adverse reactions (≥ 10%) are: diarrhea, dyspepsia, and cough. (6.1)

To report SUSPECTED ADVERSE REACTIONS, contact Digestive Care Inc. at 1-877-882-5950 or FDA at 1-800-FDA-1088 or www.fda.gov/medwatch.

FULL PRESCRIBING INFORMATION

1 INDICATIONS AND USAGE

PERTZYE® is indicated for the treatment of exocrine pancreatic insufficiency in adult and pediatric patients.

2 DOSAGE AND ADMINISTRATION

2.1 Important Dosing Information

PERTZYE is a mixture of enzymes including lipases, proteases, and amylases. PERTZYE dosing is based on lipase units.

- Use either an actual body weight or fat ingestion-based dosing scheme.
- Start at the lowest recommended dosage and individualize the dosage based on clinical symptoms, the degree of steatorrhea present, and the fat content of the diet. Changes in dosage may require an adjustment period of several days.
- Do not exceed 2,500 lipase units/kg/meal, 10,000 lipase units/kg/day, or 4,000 lipase units/g fat ingested/day in adult and pediatric patients greater than 12 months of age without further investigation [see Warnings and Precautions (5.1)].
- The total daily dosage in adult and pediatric patients greater than 12 months of age should reflect approximately three meals plus two or three snacks per day. With each snack, administer approximately half the prescribed PERTZYE dose for a meal.
- Do not substitute other pancreatic enzyme products for PERTZYE. When switching from another pancreatic enzyme product to PERTZYE, monitor patients for clinical symptoms of exocrine pancreatic insufficiency and titrate the dosage as needed.

2.2 Recommended Dosage

Adults and Pediatric Patients Greater than 12 Months of Age

The recommended oral initial starting dosage is:

- 500 lipase units/kg/meal for adult and pediatric patients 4 years of age and older.
- 1,000 lipase units/kg/meal for pediatric patients greater than 12 months to less than 4 years of age.

If signs and symptoms of malabsorption persist, increase the dosage. Titrate to either 2,500 lipase units/kg/meal, 10,000 lipase units/kg/day, or 4,000 lipase units/gram of fat ingested/day. Higher dosages may be administered if they are documented to be effective by fecal fat measures or an improvement in signs or symptoms of malabsorption including measures of nutritional status.

Pediatric Patients Birth to 12 Months of Age

The recommended oral dosage is 4,000 lipase units per 120 mL of formula or per breastfeeding.

2.3 Preparation and Administration Instructions

Adult and Pediatric Patients Greater than 12 Months of Age

Instruct adult and pediatric patients greater than 12 months of age, or their caregivers, of the following:

- Take PERTZYE with meals or snacks. If a dose is missed, take the next dose with the next meal or snack.
- Swallow capsules whole.
- For patients unable to swallow intact capsules, the capsule contents may be sprinkled on a small amount of soft acidic food with a pH of 4.5 or less (e.g., applesauce). The 4,000 USP lipase unit capsule may also be administered with applesauce via gastrostomy tube 14 French or larger.
- Do not crush or chew PERTZYE capsules or capsule contents.
- Consume sufficient liquids (water or juice) to ensure complete swallowing of PERTZYE [see Warnings and Precautions (5.2)].

Oral Administration for Patients Unable to Swallow Intact Capsules

1. Carefully open the capsules and sprinkle the entire contents on a small amount of acidic soft food (approximately 10 mL) with a pH of 4.5 or less (e.g., applesauce).
2. Mix the capsule contents with the acidic soft food (e.g., applesauce) being careful not to crush the contents.
3. Consume the entire mixture immediately. Do not save the mixture for later use.
4. Consume sufficient fluids to ensure complete swallowing of the PERTZYE food mixture.

Gastrostomy Tube Administration (14 French Gastrostomy Tube or Larger)

- Only perform gastrostomy tube administration with the contents of the 4,000 USP lipase unit capsule of PERTZYE.
- The contents of no more than two capsules may be administered at a time in the gastrostomy tube.
  1. Transfer a minimum of 10 mL of applesauce into a small bowl or medicine cup.
  2. Carefully open one or two PERTZYE 4,000 lipase unit capsules.
  3. Mix the capsule contents thoroughly with the transferred applesauce to create a uniform suspension being careful not to crush the contents. Once mixed, administer the suspension immediately.
  4. Remove the plunger from a 35 mL slip tip syringe. Cover the tip of the syringe with your finger. Transfer the PERTZYE-applesauce mixture into the syringe. Replace the plunger partially back into the syringe.
  5. Shake or tap the syringe lightly with the syringe tip facing upward so that the PERTZYE-applesauce mixture will move towards the plunger. Carefully push the plunger slowly until the residual air is removed from the syringe tip.
  6. Once the residual air is removed, connect the syringe directly into the gastrostomy tube feeding port.
  7. Push the syringe contents into the gastrostomy tube feeding port using steady pressure until empty.
  8. Draw up approximately 10 mL of water with the slip tip syringe and flush the gastrostomy tube feeding port with the water.
  9. Discard any unused portion of the PERTZYE-applesauce mixture. Do not save for later use.
  10. If dose requires more than two capsules, repeat steps 1-9 until prescribed dose is reached.

Pediatric Patients Birth to 12 Months of Age:

Instruct caregivers of pediatric patients birth to 12 months of age of the following:

- Immediately prior to each breastfeeding session or each administration of 120 mL of formula, carefully open one PERTZYE capsule (containing 4,000 USP units of lipase) and administer the entire contents using one of the following two methods:
  - Sprinkle on a small amount of acidic soft food with a pH of 4.5 or less (e.g., applesauce) being careful not to crush the capsule contents. The entire mixture should be given to the infant immediately.
  - Sprinkle the capsule contents directly into the infant's mouth.
- Immediately administer breast milk or formula after PERTZYE to ensure complete swallowing of the PERTZYE capsule contents.
- Do not crush PERTZYE capsule contents, and visually inspect the infant's mouth to ensure that no drug is retained in the mouth [see Warnings and Precautions (5.2)].
- If a dose is missed, administer the next dose with the next feeding.

3 DOSAGE FORMS AND STRENGTHS

Delayed-release capsules are available in the following strengths:

- 4,000 USP units of lipase; 14,375 USP units of protease; and 15,125 USP units of amylase in a two-piece hard gelatin capsule with a clear body printed in green with "4" and a clear cap printed with a green circular stripe and "DCI"
- 8,000 USP units of lipase; 28,750 USP units of protease; and 30,250 USP units of amylase in a two-piece hard gelatin capsule with a clear body printed in blue with "8" and a clear cap printed with a blue circular stripe and "DCI"
- 16,000 USP units of lipase; 57,500 USP units of protease; and 60,500 USP units of amylase in a two-piece hard gelatin capsule with a clear body printed in red with "16" and a clear cap printed with a red circular stripe and "DCI"
- 24,000 USP units of lipase; 86,250 USP units of protease; and 90,750 USP units of amylase in a two-piece hard gelatin capsule with a clear body printed in purple with "24" and a clear cap printed with a purple circular stripe and "DCI"

4 CONTRAINDICATIONS

None.

5 WARNINGS AND PRECAUTIONS

5.1 Fibrosing Colonopathy

Fibrosing colonopathy has been reported following treatment with pancreatic enzyme products. Fibrosing colonopathy is a rare, serious adverse reaction initially described in association with use of high-dose pancreatic enzyme products, usually with use over a prolonged period of time and most commonly reported in pediatric patients with cystic fibrosis. Pancreatic enzyme products exceeding 6,000 lipase units/kg/meal have been associated with colonic stricture, a complication of fibrosing colonopathy, in pediatric patients less than 12 years of age. The underlying mechanism of fibrosing colonopathy remains unknown.

If there is a history of fibrosing colonopathy, monitor patients during treatment with PERTZYE because some patients may be at risk of progressing to colonic stricture formation. It is uncertain whether regression of fibrosing colonopathy occurs. Do not exceed the recommended dosage of either 2,500 lipase units/kg/meal, 10,000 lipase units/kg/day, or 4,000 lipase units/g fat ingested/day in adult and pediatric patients greater than 12 months of age without further investigation. Higher dosages may be administered if they are documented to be effective by fecal fat measures or an improvement in signs and symptoms of malabsorption including measures of nutritional status. Patients receiving dosages higher than 6,000 lipase units/kg/meal should be frequently monitored for symptoms of fibrosing colonopathy and the dosage decreased or titrated downward to a lower range if clinically appropriate [see Dosage and Administration (2.1)].

5.2 Irritation of the Oral Mucosa

Crushing or chewing PERTZYE capsules or mixing the capsule contents in foods having a pH greater than 4.5 can disrupt the protective enteric coating on the capsule contents and result in early release of enzymes, irritation of the oral mucosa, and/or loss of enzyme activity.

Instruct the patient or caregiver of the following:

- Swallow capsules whole. For patients who cannot swallow the capsules whole, the capsules can be opened, and the contents sprinkled on a small amount of acidic soft food with a pH of 4.5 or less (e.g., applesauce). The 4,000 USP lipase unit capsule may also be administered with applesauce via a gastrostomy tube with a diameter of 14 French or larger.
- Do not crush or chew PERTZYE capsules or capsule contents.
- Consume sufficient liquids (juice, water, breast milk, or formula) immediately following administration of PERTZYE to ensure complete swallowing.
- Visually inspect the mouth of pediatric patients less than 12 months of age and of patients who are unable to swallow intact capsules to ensure no drug is retained in the mouth and irritation of the oral mucosa has not occurred [see Dosage and Administration (2.3)].

5.3 Hyperuricemia

Pancreatic enzyme products contain purines that may increase blood uric acid levels. High dosages have been associated with hyperuricosuria and hyperuricemia [see Overdosage (10)]. Consider monitoring blood uric acid levels in patients with gout, renal impairment, or hyperuricemia during treatment with PERTZYE.

5.4 Risk of Viral Transmission

PERTZYE is sourced from pancreatic tissue from swine used for food consumption. Although the risk that PERTZYE will transmit an infectious agent to humans has been reduced by testing for certain viruses during manufacturing and by inactivating certain viruses during manufacturing, there is a theoretical risk for transmission of viral disease, including diseases caused by novel or unidentified viruses. Thus, the presence of porcine viruses that might infect humans cannot be definitely excluded. However, no cases of transmission of an infectious illness associated with the use of porcine pancreatic extracts have been reported.

5.5 Hypersensitivity Reactions

Severe hypersensitivity reactions including anaphylaxis, asthma, hives, and pruritus have been reported with pancreatic enzyme products [see Adverse Reactions (6.2)]. If symptoms occur, initiate appropriate medical management.

Monitor patients with a known hypersensitivity reaction to proteins of porcine origin for hypersensitivity reactions during treatment with PERTZYE. The risks and benefits of continued PERTZYE treatment in patients with severe hypersensitivity reactions should be taken into consideration with the overall clinical needs of the patient.

6 ADVERSE REACTIONS

The following serious or otherwise important adverse reactions are described elsewhere in the labeling:

- Fibrosing Colonopathy [see Warnings and Precautions (5.1)]
- Irritation of the Oral Mucosa [see Warnings and Precautions (5.2)]
- Hyperuricemia [see Warnings and Precautions (5.3)]
- Risk of Viral Transmission [see Warnings and Precautions (5.4)]
- Hypersensitivity Reactions [see Warnings and Precautions (5.5)]

6.1 Clinical Trials Experience

Because clinical trials are conducted under widely varying conditions, adverse reaction rates observed in the clinical trials of a drug cannot be directly compared to the rates in the clinical trials of another drug and may not reflect the rates observed in clinical practice.

The data described below reflect exposure to PERTZYE in 21 patients, aged 8 to 43 years, with exocrine pancreatic insufficiency due to cystic fibrosis in a placebo-controlled clinical trial [see Clinical Studies (14)].

Table 1 enumerates adverse reactions that occurred in at least 2 patients (greater than or equal to 10%) treated with PERTZYE at a higher rate than with placebo.

Table 1. Adverse Reactions [Reported in at least 2 PERTZYE-treated patients (≥10%) and at a higher rate than placebo-treated patients] in a Clinical Trial of Adult and Pediatric Patients 8 Years of Age and Older with Exocrine Pancreatic Insufficiency Due to Cystic Fibrosis
Adverse Reaction | PERTZYE N=21 (%) | Placebo N=24 (%)
Diarrhea | 10% | 4%
Dyspepsia | 10% | 4%
Cough | 10% | 4%

6.2 Postmarketing Experience

The following adverse reactions have been identified during post-approval use of PERTZYE or other pancreatic enzyme products. Because these reactions are reported voluntarily from a population of uncertain size, it is not always possible to reliably estimate their frequency or establish a causal relationship to drug exposure.

Eye Disorders

- blurred vision

Gastrointestinal Disorders

- fibrosing colonopathy, distal intestinal obstruction syndrome
- abdominal pain, flatulence, constipation, and nausea

Immune System Disorders

- anaphylaxis, asthma, hives, and pruritus

Investigations

- asymptomatic elevations of liver enzymes

Musculoskeletal System

- myalgia, muscle spasm

Skin and Subcutaneous Tissue Disorders

- urticaria and rash

8 USE IN SPECIFIC POPULATIONS

8.1 Pregnancy

Risk Summary

Published data from case reports with pancrelipase use in pregnant women have not identified a drug-associated risk of major birth defects, miscarriage or other adverse maternal or fetal outcomes. Pancrelipase is minimally absorbed systematically; therefore, maternal use is not expected to result in fetal exposure to the drug. Animal reproduction studies have not been conducted with pancrelipase.

The background risk of major birth defects and miscarriage for the indicated population is unknown. All pregnancies have a background risk of birth defect, loss, or other adverse outcomes. In the U.S. general population, the estimated background risk of major birth defects and miscarriage in clinically recognized pregnancies is 2 to 4% and 15 to 20%, respectively.

8.2 Lactation

Risk Summary

There are no data on the presence of pancrelipase in either human or animal milk, the effects on the breastfed infant or the effects on milk production. Pancrelipase is minimally absorbed systemically following oral administration, therefore maternal use is not expected to result in clinically relevant exposure of breastfed infants to the drug. The developmental and health benefits of breastfeeding should be considered along with the mother's clinical need for PERTZYE and any potential adverse effects on the breastfed infant from PERTZYE or from the underlying maternal condition.

8.4 Pediatric Use

The safety and effectiveness of PERTZYE for the treatment of exocrine pancreatic insufficiency have been established in pediatric patients.

Use of PERTZYE for this indication is supported by a randomized, double-blind, placebo-controlled, crossover study of 24 pediatric patients, 8 years and older with exocrine pancreatic insufficiency due to cystic fibrosis. The safety in pediatric patients was similar to that observed in adult patients [see Adverse Reactions (6.1) and Clinical Studies (14)].

Dosages exceeding 6,000 lipase units/kg/meal have been reported postmarketing to be associated with fibrosing colonopathy and colonic strictures in pediatric patients less than 12 years of age. If there is a history of fibrosing colonopathy, monitor patients during treatment with PERTZYE because some patients may be at risk of progressing to stricture formation. Do not exceed the recommended dosage of either 2,500 lipase units/kg/meal, 10,000 lipase units/kg/day, or 4,000 lipase units/g fat ingested/day in pediatric patients greater than 12 months of age without further investigation [see Dosage and Administration (2.1) and Warnings and Precautions (5.1)].

Crushing or chewing PERTZYE capsules or mixing the capsule contents in foods having a pH greater than 4.5 can disrupt the protective enteric coating on the capsule contents and result in early release of enzymes, irritation of the oral mucosa, and/or loss of enzyme activity. Instruct the patient or caregiver of the following: consume sufficient liquids (juice, water, breast milk, or formula) to ensure complete swallowing, and visually inspect the mouth of pediatric patients less than 12 months of age to ensure that no drug is retained in the mouth and irritation of the oral mucosa has not occurred [see Dosage and Administration (2.3) and Warnings and Precautions (5.2)].

8.5 Geriatric Use

Clinical studies of PERTZYE did not include sufficient numbers of patients aged 65 years and over to determine whether they respond differently from younger patients. Other reported clinical experience has not identified differences in responses between patients aged 65 years and over and younger adult patients.

10 OVERDOSAGE

Chronic high dosages of pancreatic enzyme products have been associated with fibrosing colonopathy and colonic strictures [see Warnings and Precautions (5.1)]. High dosages of pancreatic enzyme products have been associated with hyperuricosuria and hyperuricemia [see Warnings and Precautions (5.3)].

11 DESCRIPTION

Pancrelipase is a pancreatic enzyme product consisting of a mixture of enzymes including lipases, proteases, and amylases, and is an extract derived from porcine pancreatic glands. The enteric-coated microspheres in PERTZYE are formulated to release pancreatic enzymes at an approximate pH of 5.5 or greater.

PERTZYE (pancrelipase) delayed-release capsules are for oral administration, include a two-piece hard gelatin shell containing light tan/cream-colored bicarbonate-buffered enteric-coated microspheres ranging in size from 0.8 to 1.4 mm in diameter for 4,000 USP units of lipase and 0.8 to 2.2 mm in diameter for 8,000, 16,000, and 24,000 USP units of lipase, and are available as follows:

4,000 USP units of lipase; 14,375 USP units of protease; and 15,125 USP units of amylase; delayed-release capsules have a clear body printed in green with "4" and a clear cap printed with a green circular stripe and "DCI". The imprinting ink on the capsule contains FD&C Blue #1, D&C Yellow #10, black iron oxide, dehydrated alcohol, isopropyl alcohol, butyl alcohol, propylene glycol, shellac, and ammonium hydroxide.

8,000 USP units of lipase; 28,750 USP units of protease; and 30,250 USP units of amylase; delayed-release capsules have a clear body printed in blue with "8" and a clear cap printed with a blue circular stripe and "DCI". The imprinting ink on the capsule contains FD&C Blue #1, ethanol, methanol, n-butyl alcohol, propylene glycol, shellac, and ammonium hydroxide.

16,000 USP units of lipase; 57,500 USP units of protease; and 60,500 USP units of amylase; delayed-release capsules have a clear body printed in red with "16" and a clear cap printed with a red circular stripe and "DCI". The imprinting ink on the capsule contains FD&C Red #40, povidone, titanium dioxide, dehydrated alcohol, sodium hydroxide, butyl alcohol, propylene glycol, isopropyl alcohol, and shellac.

24,000 USP units of lipase; 86,250 USP units of protease; and 90,750 USP units of amylase; delayed-release capsules have a clear body printed in purple with "24" and a clear cap printed with a purple circular stripe and "DCI". The imprinting ink on the capsule contains FD&C Blue #2, D&C Red #7, titanium dioxide, strong ammonia solution, propylene glycol, butyl alcohol, isopropyl alcohol, dehydrated alcohol, and shellac.

PERTZYE (pancrelipase) delayed-release capsules include the following inactive ingredients: cellulose acetate phthalate, diethyl phthalate, polyvinylpyrrolidone, sodium bicarbonate, sodium carbonate, sodium starch glycolate, talc, and ursodiol.

12 CLINICAL PHARMACOLOGY

12.1 Mechanism of Action

Pancreatic enzyme products contain a mixture of lipases, proteases, and amylases that catalyze the hydrolysis of fats to monoglyceride, glycerol and free fatty acids, proteins into peptides and amino acids, and starches into dextrins and short chain sugars such as maltose and maltotriose in the duodenum and proximal small intestine, thereby acting like digestive enzymes physiologically secreted by the pancreas.

12.2 Pharmacodynamics

For patients consuming a high fat diet in the clinical trials, the coefficient of fat absorption (CFA) was higher in patients who received PERTZYE compared to the placebo treatment group, indicating improved fat absorption [see Clinical Studies (14)].

12.3 Pharmacokinetics

Following oral administration, the lipases, proteases, and amylases released from PERTZYE are not absorbed from the gastrointestinal tract in appreciable amounts.

Drug Interactions

The lipases, proteases, and amylases of PERTZYE are not substrates of CYP enzymes or transporters. CYP enzyme or transporter mediated drug interactions are not expected.

14 CLINICAL STUDIES

Adult and Pediatric Patients

A randomized, double-blind, placebo-controlled, crossover study was conducted in 24 patients aged 8 to 43 years (mean age of 20 years) with exocrine pancreatic insufficiency due to cystic fibrosis. Patients were randomized to receive PERTZYE at individually titrated doses (not to exceed 2,500 lipase units/kg/meal) or matching placebo for 6 to 8 days of treatment, followed by crossover to the alternate treatment for an additional 6 to 8 days. The mean lipase dosage during the treatment period was 1,565 lipase units/kg/meal and a controlled high-fat diet (approximately 2g fat/kg/day) was maintained throughout the study. The length of exposure to PERTZYE during this study was 20 to 28 days, including the treatment period of 6 to 8 days, and the open label titration and transition periods of 7 to 10 days each.

The efficacy analysis population included 21 patients who completed both double-blind treatment periods.

Coefficient of Fat Absorption Endpoint and Results

The primary efficacy endpoint was the mean difference in coefficient of fat absorption (CFA) between PERTZYE and placebo treatment. The CFA was determined by a 72-hour stool collection during both treatments, when both fat ingestion and excretion were measured.

Mean CFA was 83% with PERTZYE treatment compared to 46% with placebo treatment. The mean difference in CFA was 36 percentage points in favor of PERTZYE treatment with 95% CI: (28, 45) and p<0.001.

Coefficient of Nitrogen Absorption Endpoint and Results

The coefficient of nitrogen absorption (CNA) was determined by a 72-hour stool collection during both treatments, when nitrogen excretion was measured and nitrogen ingestion from a controlled diet was estimated (based on the assumption that proteins contain 16% nitrogen). Each patient's CNA during placebo treatment was used as their no-treatment CNA value.

Mean CNA was 79% with PERTZYE treatment compared to 47% with placebo treatment. The mean difference in CNA was 32 percentage points in favor of PERTZYE treatment and this was a statistically significant change.

There were no differences between pediatric patients and adults in the severity of pancreatic insufficiency (placebo response) or in the magnitude of the response to PERTZYE.

16 HOW SUPPLIED/STORAGE AND HANDLING

PERTZYE (pancrelipase) delayed-release capsules, containing light tan/cream-colored delayed-release microspheres are supplied as follows:

Strength | Description | Supplied As | NDC Number
4,000 USP units of lipase; 14,375 USP units of protease; 15,125 USP units of amylase | Two-piece hard gelatin capsule with a clear body printed in green with "4" and a clear cap printed with a green circular stripe and "DCI" | Bottles of 100 | 59767-004-01
8,000 USP units of lipase; 28,750 USP units of protease; 30,250 USP units of amylase | Two-piece hard gelatin capsule with a clear body printed in blue with "8" and a clear cap printed with a blue circular stripe and "DCI" | Bottles of 100 Bottles of 250 | 59767-008-01 59767-008-02
16,000 USP units of lipase; 57,500 USP units of protease; 60,500 USP units of amylase | Two-piece hard gelatin capsule with a clear body printed in red with "16" and a clear cap printed with a red circular stripe and "DCI" | Bottles of 100 Bottles of 250 | 59767-016-01 59767-016-02
24,000 USP units of lipase; 86,250 USP units of protease; 90,750 USP units of amylase | Two-piece hard gelatin capsule with a clear body printed in purple with "24" and a clear cap printed with a purple circular stripe and "DCI" | Bottles of 80 Bottles of 200 | 59767-024-01 59767-024-02

Storage and Handling

- Store PERTZYE at room temperature 20°C to 25°C (68°F to 77°F), excursions permitted to 15°C to 40°C (59°F to 104°F) for up to 30 days. PERTZYE hard gelatin capsules should be stored in a dry place in the original container or equivalent airtight container. After opening, keep the container tightly closed between uses to protect from moisture.
- PERTZYE is dispensed in bottles containing a desiccant.

17 PATIENT COUNSELING INFORMATION

Advise the patient or caregiver to read the FDA-approved patient labeling (Medication Guide and Instructions for Use).

Fibrosing Colonopathy

Advise the patient or caregiver that fibrosing colonopathy has been reported with high dosages of pancreatic enzyme products, usually with use over a prolonged period of time and in pediatric patients less than 12 years of age. Advise patients and caregivers that if signs and symptoms of colon stricture formation occur (e.g., stomach area (abdominal) pain, bloating, trouble passing stool (constipation), nausea, vomiting, diarrhea) to immediately contact their healthcare provider [see Warnings and Precautions (5.1)].

Hyperuricemia

Advise the patient or caregiver that hyperuricemia may occur in patients with gout or renal impairment and to contact the healthcare provider if they experience pain, stiffness, redness or swelling of their joints [see Warnings and Precautions (5.3)].

Hypersensitivity Reactions

Inform the patient or caregiver that severe hypersensitivity reactions, including anaphylaxis, asthma, hives, and pruritus, have been reported with use of pancreatic enzyme products. Seek medical attention if signs or symptoms of a hypersensitivity reaction develop [see Warnings and Precautions (5.5)].

Dosage

Advise the patient or caregiver to take or administer PERTZYE as prescribed, and to contact the healthcare provider if signs and symptoms of malabsorption persist [see Dosage and Administration (2.2)].

Administration

Instruct the patient or caregiver to:

- Take PERTZYE with meals or snacks.
- Swallow capsules whole.
- For patients unable to swallow intact capsules:
  - the capsule contents may be sprinkled on a small amount of soft acidic food with a pH of 4.5 or less (e.g., applesauce). The 4,000 USP lipase unit capsule may also be administered with applesauce via gastrostomy tube 14 French or larger.
  - For pediatric patients birth to 12 months of age, PERTZYE capsules can be opened, and the capsule contents sprinkled directly into the infant's mouth.
  - See the Instructions for Use for a description of all preparation and administration instructions.
- Consume sufficient liquids (juice, water, breast milk, or formula) and visually inspect an infant's mouth to ensure complete swallowing of PERTZYE capsules or capsule contents [see Warnings and Precautions (5.2)].
- Do not crush or chew PERTZYE capsules or capsule contents.
- Do not mix the PERTZYE capsule contents directly into a bottle of breast milk or formula.

Storage

Instruct the patient or caregiver as follows:

- Keep PERTZYE in a dry place and protect from moisture and heat.
- After opening, keep the container tightly closed between uses to protect from moisture.
- The desiccant packet should not be eaten or thrown away.

Manufactured by:
Digestive Care, Inc.
1120 Win Drive
Bethlehem, PA 18017
U.S. License No. 2184
Product of USA

PERTZYE® is a registered trademark of Digestive Care, Inc.
U.S. Patent Numbers: 5,260,074; 5,302,400; 5,324,514; 5,460,812; 5,578,304; 5,750,104

MEDICATION GUIDE
PERTZYE (pert-zye)
(pancrelipase)
delayed-release capsules

What is the most important information I should know about PERTZYE?
PERTZYE may increase the risk of having a rare bowel disorder called fibrosing colonopathy, especially if taken at a high dose for a long time in children with cystic fibrosis. This condition is serious and may require surgery. The risk of having this condition may be reduced by following the dosing instructions that your doctor gives you.
Call your doctor right away if you have any unusual or severe:

- stomach area (abdominal) pain
- bloating
- trouble passing stool (constipation)

- nausea
- vomiting
- diarrhea

Take PERTZYE exactly as prescribed by your doctor. Do not take more PERTZYE than directed by your doctor.

What is PERTZYE?

- PERTZYE is a prescription medicine used to treat people who cannot digest food normally because their pancreas does not make enough enzymes.
- PERTZYE capsules contain a mixture of digestive enzymes including lipases, proteases and amylases from pig pancreas.
- PERTZYE is safe and effective in adults and children.

Before taking PERTZYE, tell your doctor about all of your medical conditions, including if you:

- are allergic to pork (pig) products.
- have a history of blockage of your intestines or scarring or thickening of your bowel wall (fibrosing colonopathy).
- have gout, kidney disease, or high blood uric acid (hyperuricemia).
- have trouble swallowing capsules.
- have any other medical condition.
- are pregnant or plan to become pregnant.
- are breastfeeding or plan to breastfeed. It is not known if PERTZYE passes into your breast milk. Talk to your doctor about the best way to feed your baby if you take PERTZYE.

Tell your doctor about all the medicines you take, including prescription and over-the-counter medicines, vitamins, and herbal supplements.
Know the medicines you take. Keep a list of them and show it to your doctor and pharmacist when you get a new medicine.

How should I take PERTZYE?

- See the Instructions for Use at the end of this Medication Guide for detailed instructions about how to give PERTZYE by mouth and through a gastrostomy tube.
- Take PERTZYE capsules exactly as your doctor tells you. Contact your doctor if you continue to have signs and symptoms of malabsorption (not absorbing nutrients from food) such as abdominal pain, abdominal bloating, fatty stools, or weight loss. Your dose may need to be changed.
- You should not switch PERTZYE with any other pancreatic enzyme product without first talking with your doctor.
- Do not take more capsules in a day than the number your doctor tells you to take (total daily dose).
- Always take PERTZYE with a meal or snack. If you eat a lot of meals or snacks in a day, be careful not to go over your total daily dose.
- Your doctor may change your dose based on the amount of fatty foods you eat or based on your weight.
- PERTZYE capsules should be swallowed whole. Do not crush or chew the PERTZYE capsules or their contents and do not hold the capsule or capsule contents in your mouth. Crushing or chewing the PERTZYE capsules may cause irritation in your mouth or change the way PERTZYE works in your body.
- Drink plenty of liquid to ensure complete swallowing of the PERTZYE capsules or PERTZYE capsule contents-food mixture.
- Throw away the PERTZYE capsule contents-food mixture that is not used. Do not save this mixture for later use.
- If you miss a dose of PERTZYE, wait until your next meal or snack and take your prescribed dose. Take your next dose at your usual time. Do not take two doses at one time.

What are the possible side effects of PERTZYE?

- See "What is the most important information I should know about PERTZYE?"
- Irritation of the inside of your mouth. This can happen if PERTZYE is not swallowed completely, is crushed or chewed, or is mixed in foods that are not recommended.
- Increase in blood uric acid levels (hyperuricemia). This may happen in people with gout, kidney problems, or those who take high doses of pancrelipase, the active ingredient in PERTZYE. Call your doctor if you have pain, stiffness, redness or swelling in your joints.
- Severe allergic reactions. Severe allergic reactions have happened in people taking pancreatic enzyme products like PERTZYE. Stop taking PERTZYE and get emergency treatment right away if you have any of these symptoms: trouble with breathing, skin rashes, swollen lips or itching.

The most common side effects of PERTZYE include:

- diarrhea
- upset stomach (indigestion)

- cough

Other possible side effects:
PERTZYE and other pancreatic enzyme products are made from the pancreas of pigs, the same pigs people eat as pork. These pigs may carry viruses. Although it has never been reported, it may be possible for a person to get a viral infection from taking pancreatic enzyme products that come from pigs.
Tell your doctor if you have any side effect that bothers you or that does not go away.
These are not all of the possible side effects of PERTZYE. For more information, ask your doctor or pharmacist.
Call your doctor for medical advice about side effects. You may report side effects to FDA at 1-800-FDA-1088.

How should I store PERTZYE?

- Store PERTZYE at room temperature between 68ºF to 77ºF (20°C to 25°C).
- Keep PERTZYE in a dry place and in the original container or equivalent airtight container.
- After opening the bottle, keep it tightly closed between uses to keep your medicine dry (protect it from moisture).
- The PERTZYE bottle contains a desiccant packet to help keep your medicine dry. Do not eat or throw away the desiccant packet in your medicine bottle.

Keep PERTZYE and all medicines out of the reach of children.

General information about the safe and effective use of PERTZYE.
Medicines are sometimes prescribed for purposes other than those listed in a Medication Guide. Do not use PERTZYE for a condition for which it was not prescribed. Do not give PERTZYE to other people, even if they have the same symptoms that you have. It may harm them. You can ask your pharmacist or doctor for information about PERTZYE that is written for health professionals.

What are the ingredients in PERTZYE?
Active ingredients: lipase, protease, and amylase.
Inactive ingredients: cellulose acetate phthalate, diethyl phthalate, polyvinylpyrrolidone, sodium bicarbonate, sodium carbonate, sodium starch glycolate, talc, and ursodiol.
The hard gelatin capsule shells contain: gelatin and water.
The green imprinting ink on the 4,000 units of lipase; 14,375 units of protease; 15,125 units of amylase capsules contain: FD&C Blue #1, D&C Yellow #10, black iron oxide, dehydrated alcohol, isopropyl alcohol, butyl alcohol, propylene glycol, shellac and ammonium hydroxide.
The blue imprinting ink on the 8,000 units of lipase; 28,750 units of protease; 30,250 units of amylase capsules contain: FD&C Blue #1, ethanol, methanol, n-butyl alcohol, propylene glycol, shellac and ammonium hydroxide.
The red imprinting ink on the 16,000 units of lipase; 57,500 units of protease; 60,500 units of amylase capsules contain: FD&C Red #40, povidone, titanium dioxide, dehydrated alcohol, sodium hydroxide, butyl alcohol, propylene glycol, isopropyl alcohol, and shellac.
The purple imprinting ink on the 24,000 units of lipase; 86,250 units of protease; 90,750 units of amylase capsules contain: FD&C Blue #2, D&C Red #7, titanium dioxide, strong ammonia solution, propylene glycol, butyl alcohol, isopropyl alcohol, dehydrated alcohol, and shellac.
For more information, go to www.Pertzye.com or call 1-877-882-5950.

Manufactured by:
Digestive Care, Inc.
1120 Win Drive
Bethlehem, PA 18017
U.S. License No. 2184
Product of USA

This Medication Guide has been approved by the U.S. Food and Drug Administration.

Revised: 02/2024

INSTRUCTIONS FOR USE
PERTZYE (pert-zye)
(pancrelipase)
delayed-release capsules

This Instructions for Use contains information on how to give PERTZYE by mouth and through a gastrostomy tube.

Important Information You Need to Know Before Taking PERTZYE:

- Always take PERTZYE with a meal or snack.
- PERTZYE capsules should be swallowed whole. Do not crush or chew the PERTZYE capsules or their contents, and do not hold the capsule or capsule contents in your mouth.
- Drink plenty of liquid to ensure complete swallowing of PERTZYE capsules or PERTZYE capsule contents-food mixture.
- Throw away the PERTZYE capsule contents-food mixture that is not used. Do not save this mixture for later use.

Giving PERTZYE to infants (Children from Birth to 12 Months of Age) by mouth:

The two methods to give PERTZYE to Infants (Children from Birth to 12 Months of Age) are described below:

a) Giving with Applesauce Before Breast or Formula Feeding

1. Place about 2 teaspoons of applesauce, the kind found in baby food jars that you buy at the store, or other food recommended by your doctor, into a clean container.
2. Carefully open the PERTZYE capsule by grasping and slightly squeezing both ends of the capsule and then twisting and pulling the capsule apart. Pour the capsule contents onto the food in the clean container. Throw away the empty PERTZYE capsule.
3. Carefully mix the capsule contents evenly through the food. Be careful not to crush the PERTZYE capsule contents when mixing.
4. Give the PERTZYE capsule contents-food mixture to your infant right away.
5. Give your infant 4 ounces (120 mL) of formula or breastfeed your infant right away.
6. Look in your infant's mouth to make sure that all of the medicine is swallowed and there is no PERTZYE capsule contents-food mixture left in your infant's mouth.

b) Giving Directly into the Infant's Mouth Before Breast or Formula Feeding

1. Carefully open the PERTZYE capsule by grasping and slightly squeezing both ends of the capsule and then twisting and pulling the capsule apart. Empty the capsule contents into your infant's mouth.
2. Give your infant 4 ounces (120 mL) of formula or breastfeed right away.
3. Look in your infant's mouth to make sure that all of the medicine is swallowed and there is no PERTZYE capsule contents left in your infant's mouth.
4. Throw away the empty PERTZYE capsule.

Do not mix the PERTZYE capsule contents directly into a bottle of breast milk or formula.

Giving PERTZYE to children and adults by mouth:

- Swallow PERTZYE capsules whole and take them with enough liquid to swallow them right away.
- If you have trouble swallowing capsules, follow these instructions for taking PERTZYE with food:
  1. Place about 2 teaspoons of applesauce, or other food recommended by your doctor, into a clean container.
  2. Carefully open the capsules that you will need for the prescribed dose by grasping and slightly squeezing both ends of the capsule and then twisting and pulling the capsule apart. Pour the capsule contents onto the food in the clean container.
  3. Throw away the empty PERTZYE capsules.
  4. Carefully mix the capsule contents evenly through the food. Be careful not to crush the PERTZYE capsule contents when mixing.
  5. Swallow all of the PERTZYE capsule contents-food mixture right away.
  6. Drink plenty of water or juice to make sure that all of the medicine is swallowed and there is no PERTZYE capsule contents-food mixture left in the mouth.

Giving PERTZYE through a gastrostomy tube:

- PERTZYE 4,000 lipase units capsule contents may be given through a gastrostomy tube that is size 14 French or larger. Do not give PERTZYE through a gastrostomy tube smaller than size 14 French.
- Do not give more than the contents of 2 PERTZYE 4,000 lipase units capsules through a gastrostomy tube at a time.
- Give the PERTZYE capsule contents-food mixture right away after it is prepared.
  1. Place at least 2 teaspoons of applesauce, or other food recommended by your doctor, into a clean container.
  2. Carefully open 1 or 2 of the PERTZYE capsules, depending on your prescribed dose, by grasping and slightly squeezing both ends of the capsule and then twisting and pulling the capsule apart. Pour the capsule contents onto the food in the clean container. Throw away the empty PERTZYE capsules (See Figure A).
    Figure A
  3. Carefully mix the capsule contents evenly through the food. Be careful not to crush the PERTZYE capsule contents when mixing.
  4. Remove the plunger from a 35 mL slip tip syringe. Cover the tip of the syringe with your finger.
  5. Carefully spoon the PERTZYE capsule contents-food mixture into the slip tip syringe (See Figure B).
    Figure B
  6. Replace the plunger partially back into the slip tip syringe.
  7. Turn the slip tip syringe so the syringe tip is facing upward. Remove your finger from the tip of the slip tip syringe.
  8. Gently shake or tap the slip tip syringe so that the PERTZYE capsule contents-food mixture moves down towards the plunger.
  9. Carefully push up slowly on the plunger until the PERTZYE capsule contents-food mixture fills the syringe tip (See Figure C).
    Figure C
  10. Connect the slip tip syringe directly into the gastrostomy tube feeding port.
  11. Press on the plunger of the slip tip syringe using steady pressure to push all of the PERTZYE capsule contents-food mixture into the gastrostomy tube feeding port over 10 seconds to 12 seconds (See Figure D).
    Figure D
  12. Flush the gastrostomy tube feeding port with about 10 mL of water.
  13. If your prescribed dose is more than 2 capsules of PERTZYE, repeat steps 1 through 12, using only 1 or 2 PERTZYE capsules at a time, until the prescribed dose is given.

Storing PERTZYE:

- Store PERTZYE at room temperature between 68ºF to 77ºF (20°C to 25°C).
- Keep PERTZYE in a dry place and in the original container or equivalent airtight container.
- After opening the bottle, keep it tightly closed between uses to keep your medicine dry (protect it from moisture).
- The PERTZYE bottle contains a desiccant packet to help keep your medicine dry. Do not eat or throw away the desiccant packet in your medicine bottle.

Keep PERTZYE and all medicines out of the reach of children.

Manufactured by:
Digestive Care, Inc.
1120 Win Drive
Bethlehem, PA 18017
U.S. License No. 2184
Product of USA
© 2024 Digestive Care, Inc.

This Instructions for Use has been approved by the U.S. Food and Drug Administration.
Revised: 02/2024

PRINCIPAL DISPLAY PANEL - 100 Capsule Bottle Label - 59767-008-01

100 Capsules
NDC 59767-008-01

pancrelipase
PERTZYE®

Rx Only

Delayed-Release Capsules

DOSE BY
LIPASE
UNITS

Lipase
8,000 USP Units

Protease
28,750 USP Units

Amylase
30,250 USP Units

Each delayed-release capsule contains pancrelipase
in bicarbonate-buffered enteric-coated microspheres.

This product is of porcine origin. No preservative.

PHARMACIST: Dispense the accompanying
Medication Guide to each patient.

PRINCIPAL DISPLAY PANEL - 100 Capsule Bottle Label - 59767-004-01

100 Capsules
NDC 59767-004-01

pancrelipase
PERTZYE®

Rx Only

Delayed-Release Capsules

DOSE BY
LIPASE
UNITS

Lipase
4,000 USP Units

Protease
14,375 USP Units

Amylase
15,125 USP Units

Each delayed-release capsule contains pancrelipase
in bicarbonate-buffered enteric-coated microspheres.

This product is of porcine origin. No preservative.

PHARMACIST: Dispense the accompanying
Medication Guide to each patient.

PRINCIPAL DISPLAY PANEL - 100 Capsule Bottle Label - 59767-016-01

100 Capsules
NDC 59767-016-01

pancrelipase
PERTZYE®

Rx Only

Delayed-Release Capsules

DOSE BY
LIPASE
UNITS

Lipase
16,000 USP Units

Protease
57,500 USP Units

Amylase
60,500 USP Units

Each delayed-release capsule contains pancrelipase
in bicarbonate-buffered enteric-coated microspheres.

This product is of porcine origin. No preservative.

PHARMACIST: Dispense the accompanying
Medication Guide to each patient.

PRINCIPAL DISPLAY PANEL - 80 Capsule Bottle Label

80 Capsules
NDC 59767-024-01

pancrelipase
PERTZYE®

Rx Only

Delayed-Release Capsules

DOSE BY
LIPASE
UNITS

Lipase
24,000 USP Units

Protease
86,250 USP Units

Amylase
90,750 USP Units

Each delayed-release capsule contains pancrelipase
in bicarbonate-buffered enteric-coated microspheres.

This product is of porcine origin. No preservative.

PHARMACIST: Dispense the accompanying
Medication Guide to each patient.